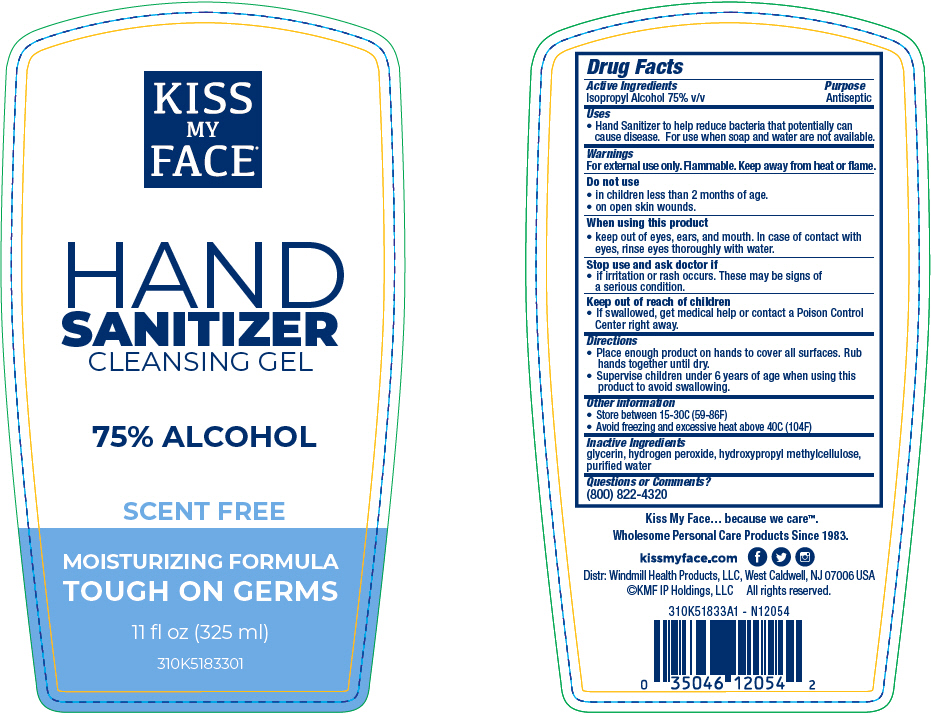 DRUG LABEL: Kiss My Face Hand Sanitizer Cleansing Alcohol Scent Free
NDC: 74154-008 | Form: GEL
Manufacturer: Windmill Health Products, LLC
Category: otc | Type: HUMAN OTC DRUG LABEL
Date: 20220204

ACTIVE INGREDIENTS: Isopropyl Alcohol 75 mL/100 mL
INACTIVE INGREDIENTS: GLYCERIN; HYDROGEN PEROXIDE; HYPROMELLOSE, UNSPECIFIED; WATER

Kiss My Face® Hand Sanitizer Cleansing Alcohol Scent Free

Drug Facts

Active Ingredients

Isopropyl Alcohol 75% v/v

Purpose

Antiseptic

Uses

- Hand Sanitizer to help reduce bacteria that potentially can cause disease. For use when soap and water are not available.

Warnings

For external use only. Flammable. Keep away from heat or flame.

Do not use

- in children less than 2 months of age.
- on open skin wounds.

When using this product

- keep out of eyes, ears, and mouth. In case of contact with eyes, rinse eyes thoroughly with water.

Stop use and ask doctor if

- if irritation or rash occurs. These may be signs of a serious condition.

Keep out of reach of children

- If swallowed, get medical help or contact a Poison Control Center right away.

Directions

- Place enough product on hands to cover all surfaces. Rub hands together until dry.
- Supervise children under 6 years of age when using this product to avoid swallowing.

Other information

- Store between 15-30C (59-86F)
- Avoid freezing and excessive heat above 40C (104F)

Inactive Ingredients

glycerin, hydrogen peroxide, hydroxypropyl methylcellulose, purified water

Questions or Comments?

(800) 822-4320

PRINCIPAL DISPLAY PANEL - 325 ml Bottle Label

KISS
MY
FACE®

HAND
SANITIZER
CLEANSING GEL

75% ALCOHOL

SCENT FREE

MOISTURIZING FORMULA

TOUGH ON GERMS

11 fl oz (325 ml)

310K5183301